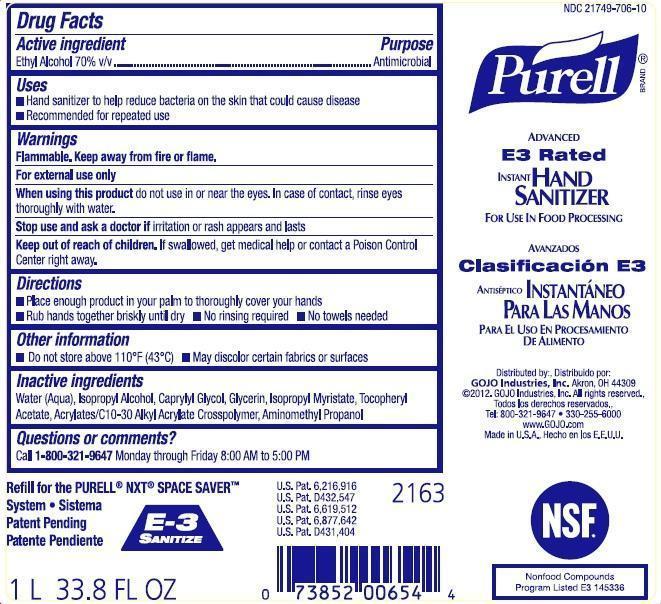 DRUG LABEL: PURELL Advanced E3 Rated Instant Hand Sanitizer
NDC: 21749-706 | Form: LIQUID
Manufacturer: GOJO Industries, Inc.
Category: otc | Type: HUMAN OTC DRUG LABEL
Date: 20260112

ACTIVE INGREDIENTS: ALCOHOL 0.7 mL/1 mL
INACTIVE INGREDIENTS: WATER; ISOPROPYL ALCOHOL; GLYCERIN; ISOPROPYL MYRISTATE; .ALPHA.-TOCOPHEROL ACETATE, D-; CAPRYLYL GLYCOL; AMINOMETHYLPROPANOL

PURELL Advanced E3 Rated Instant Hand Sanitizer

Active ingredient

Ethyl Alcohol 70% v/v

Purpose

Antimicrobial

Uses

- Hand sanitizer to help reduce bacteria on the skin that could cause disease
- Recommended for repeated use

Warnings

Flammable. Keep away from fire or flame.

For external use only

WHEN USING

When using this productdo not use in or near the eyes. In case of contact, rinse eyes thoroughly with water.

Stop use and ask a doctor ifirritation or rash appears and lasts

Keep out of reach of children.If swallowed, get medical help or contact a Poison Control Center right away.

Directions

- Place enough product in your palm to thoroughly cover your hands
- Rub hands together briskly until dry
- No rinsing required
- No towels needed

Inactive ingredients

Water (Aqua), Isopropyl Alcohol, Caprylyl Glycol, Glycerin, Isopropyl Myristate, Tocopheryl Acetate, Acrylates/C10-30 Alkyl Acrylate Crosspolymer, Aminomethyl Propanol